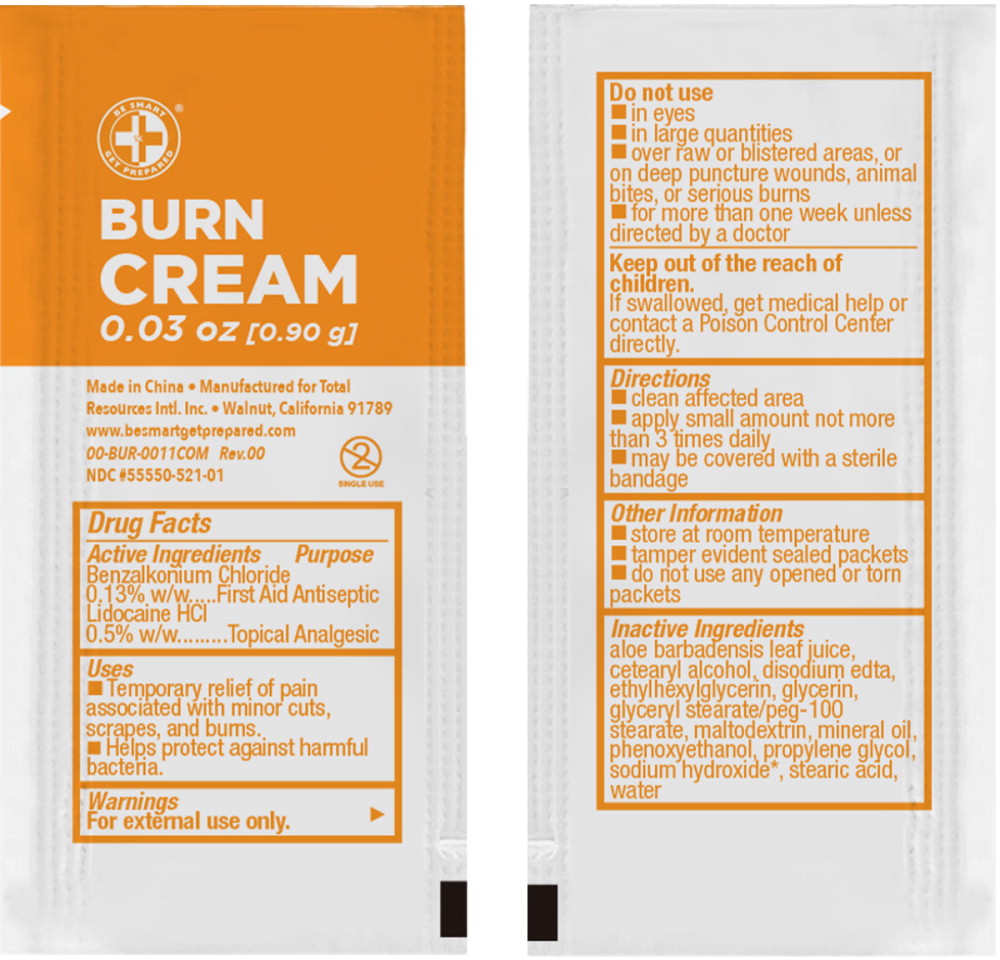 DRUG LABEL: Be Smart Get Prepared Burn Cream
NDC: 55550-521 | Form: CREAM
Manufacturer: Total Resources International, Inc
Category: otc | Type: HUMAN OTC DRUG LABEL
Date: 20240816

ACTIVE INGREDIENTS: BENZALKONIUM CHLORIDE 0.13 g/100 g; LIDOCAINE HYDROCHLORIDE ANHYDROUS 0.5 g/100 g
INACTIVE INGREDIENTS: ALOE VERA LEAF; CETOSTEARYL ALCOHOL; GLYCERIN; WATER; EDETATE DISODIUM ANHYDROUS; ETHYLHEXYLGLYCERIN; GLYCERYL STEARATE/PEG-100 STEARATE; MALTODEXTRIN; PHENOXYETHANOL; PROPYLENE GLYCOL; STEARIC ACID; MINERAL OIL; SODIUM HYDROXIDE

Drug Facts

Active Ingredients

Benzalkonium Chloride 0.13% w/w

Lidocaine HCl 0.5% w/w

Purpose

First Aid Antiseptic

Topical Analgesic

Uses

- Temporary relief of pain associated with minor cuts, scrapes, and burns.
- Helps protect against harmful bacteria.

Warnings

For external use only.

Do not use

- in eyes
- in large quantities
- over raw or blistered areas, or on deep puncture wounds, animal bites, or serious burns
- for more than one week unless directed by a doctor

Keep out of reach of children.

If swallowed, get medical help or contact a Poison Control Center directly.

Directions

- clean affected area
- apply small amount not more than 3 times daily
- may be covered with a sterile bandage

Other Information

- store at room temperature
- tamper evident sealed packets
- do not use any opened or torn packets

Inactive Ingredients

aloe barbadensis leaf juice, cetearyl alcohol, disodium edta, ethylhexylglycerin, glycerin, glyceryl stearate/peg-100 stearate, maltodextrin, mineral oil, phenoxyethanol, propylene glycol, stearic acid, sodium hydroxide, water

Principal Display Panel – 0.90mL Pouch Label

BE SMART

GET PREPARED®

BURN CREAM

0.03 oz [0.90 g]

Single Use

Made in China

Manufactured for Total Resources Intl. Inc.

Walnut, California 91789

www.besmartgetprepared.com • 00-BUR-0011COM Rev. 00

NDC 55550-521-01